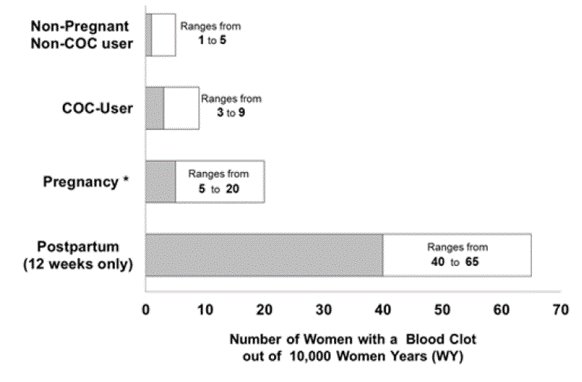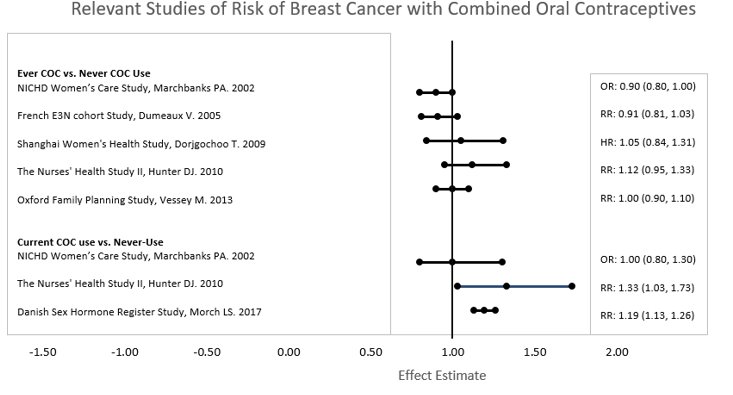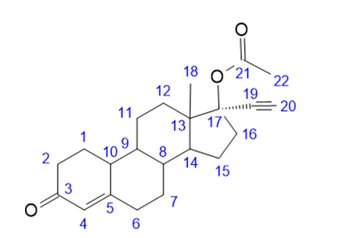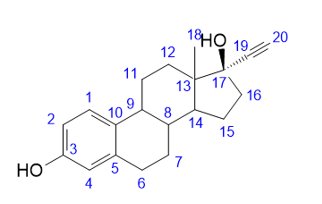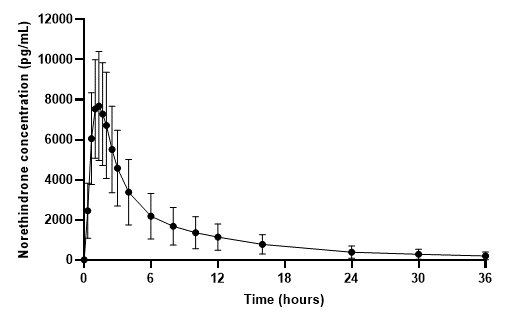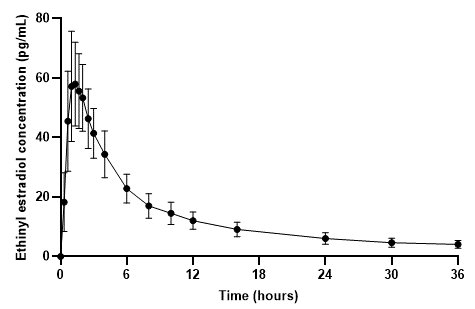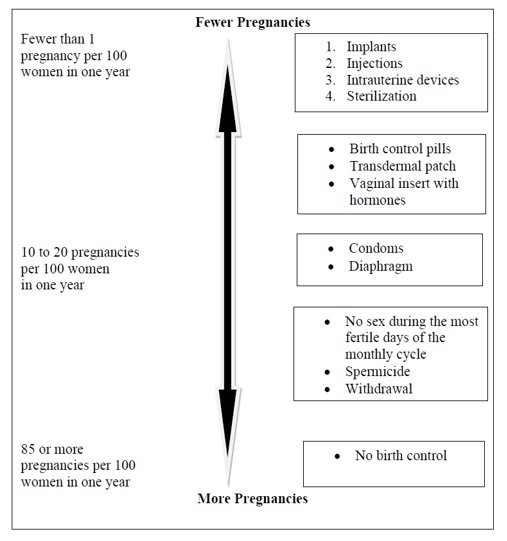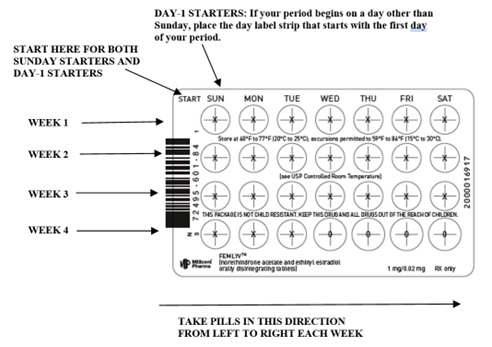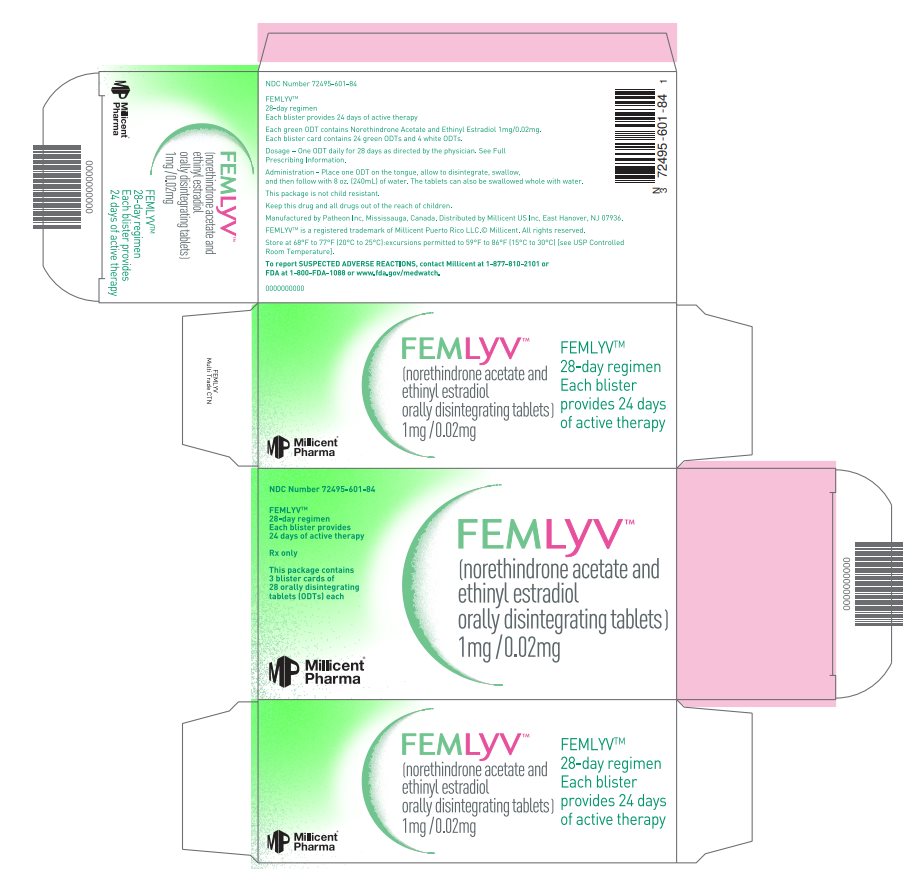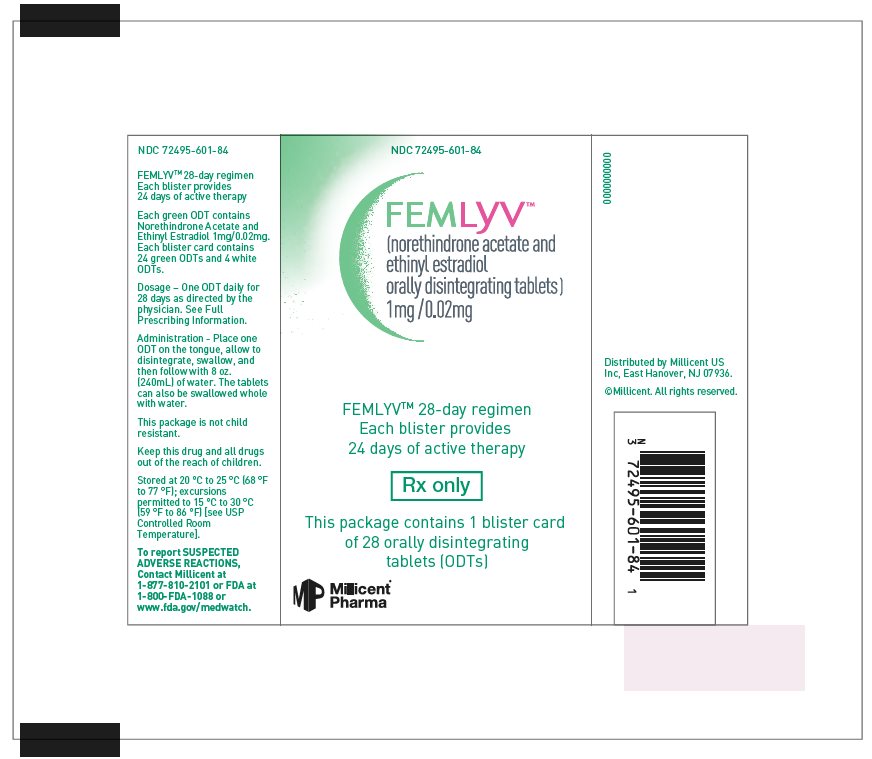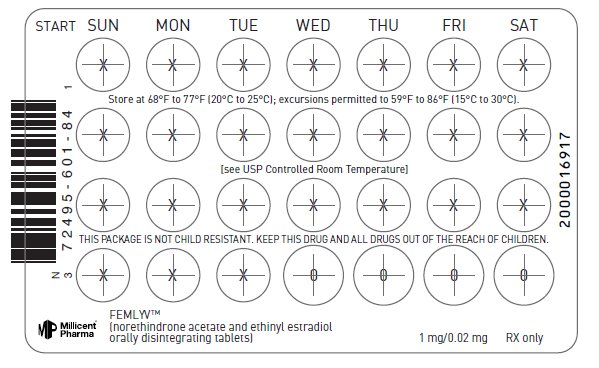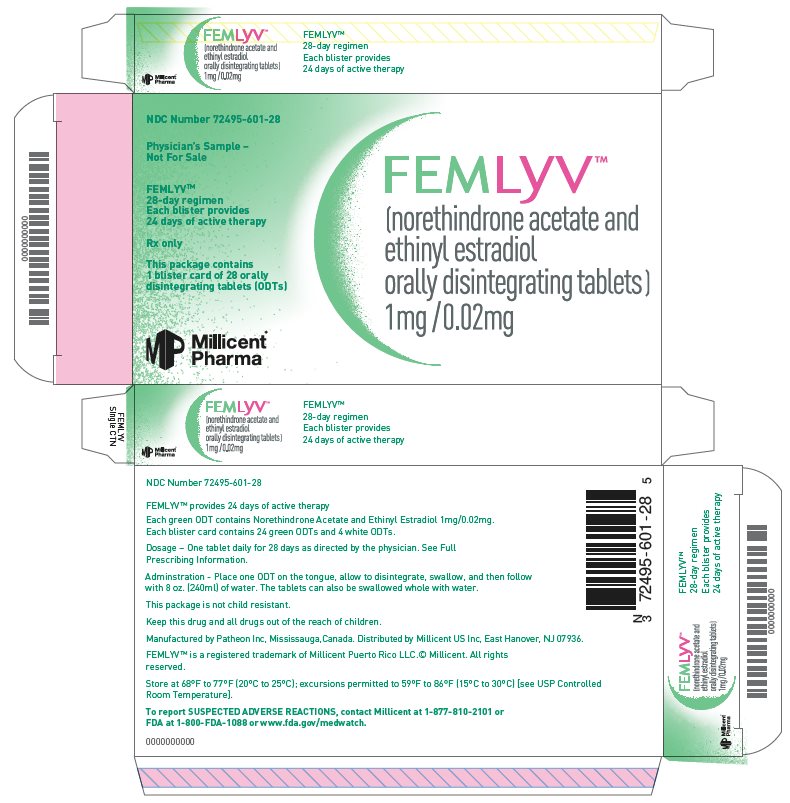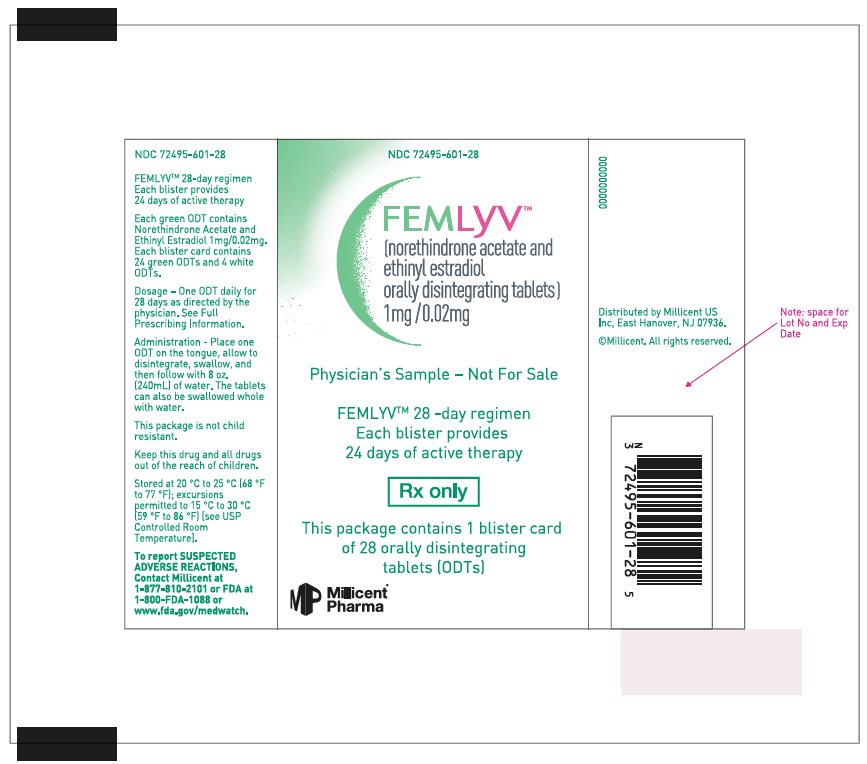 DRUG LABEL: FEMLYV
NDC: 72495-601 | Form: KIT | Route: ORAL
Manufacturer: Millicent US, Inc.
Category: prescription | Type: HUMAN PRESCRIPTION DRUG LABEL
Date: 20250903

ACTIVE INGREDIENTS: NORETHINDRONE ACETATE 1 mg/1 1; ETHINYL ESTRADIOL 20 ug/1 1
INACTIVE INGREDIENTS: MICROCRYSTALLINE CELLULOSE; WATER; ALCOHOL; MANNITOL; FD&C BLUE NO. 1 ALUMINUM LAKE; D&C YELLOW NO. 10 ALUMINUM LAKE; MAGNESIUM STEARATE; SPEARMINT; SUCRALOSE; .ALPHA.-TOCOPHEROL; CROSCARMELLOSE SODIUM; STARCH, CORN; MICROCRYSTALLINE CELLULOSE; WATER; ALCOHOL; MANNITOL; D&C YELLOW NO. 10; SPEARMINT; SUCRALOSE; STARCH, CORN; CROSCARMELLOSE SODIUM

HIGHLIGHTS OF PRESCRIBING INFORMATION

These highlights do not include all the information needed to use FEMLYV™ safely and effectively. See full prescribing information for FEMLYV.
FEMLYV (norethindrone acetate and ethinyl estradiol orally disintegrating tablets)
Initial U.S. Approval: 1968

RECENT MAJOR CHANGES

Dosage and Administration, Dosing FEMLYV (2.1) | XX/2025

WARNING: CIGARETTE SMOKING AND SERIOUS CARDIOVASCULAR EVENTS

See full prescribing information for complete boxed warning.

- Women over 35 years old who smoke should not use FEMLYV (4)
- Cigarette smoking increases the risk of serious cardiovascular events from combination oral contraceptive (COC) use (4)

1 INDICATIONS AND USAGE

FEMLYV is a combination of norethindrone acetate, a progestin, and ethinyl estradiol, an estrogen, indicated for use by females of reproductive potential to prevent pregnancy (1)
Limitations of Use
The efficacy in females of reproductive potential with a body mass index of more than 35 kg/m^2 has not been evaluated (1, 8.8)

2 DOSAGE AND ADMINISTRATION

- Place one FEMLYV orally disintegrating tablet (ODT) on the tongue, allow to disintegrate and then follow with 8 oz. (240 mL) of water.
- The tablets can also be swallowed whole with 8 oz. (240 mL) of water.
- Take at the same time daily without regards to meals (2.1, 12.3)
- Take ODTs in the order directed on the blister pack (2.1)

3 DOSAGE FORMS AND STRENGTHS

Orally disintegrating tablets (3):

- 24 ODTs each containing 1 mg norethindrone acetate and 0.02 mg ethinyl estradiol
- 4 inert ODTs

4 CONTRAINDICATIONS

- A high risk of arterial or venous thrombotic diseases (4)
- Breast cancer or history of breast cancer (4)
- Liver tumors, benign or malignant, or hepatic impairment (4)
- Co-administration with Hepatitis C drug combinations containing ombitasvir/paritaprevir/ritonavir, with or without dasabuvir (4)
- Undiagnosed abnormal uterine bleeding (4)

5 WARNINGS AND PRECAUTIONS

- Thromboembolic Disorders and Other Vascular Problems: Discontinue FEMLYV if a thrombotic event occurs. Discontinue at least 4 weeks before through 2 weeks after major surgery. Start no earlier than 4 weeks after delivery, in women who are not breastfeeding. Consider all cardiovascular risk factors before initiating in any female, particularly in the presence of multiple risk factors (5.1)
- High blood pressure: Monitor blood pressure periodically and stop use if blood pressure rises significantly. Do not prescribe for women with uncontrolled hypertension or hypertension with vascular disease (5.2)
- Migraine: Evaluate significant change in migraines and discontinue if new, recurrent, persistent, or severe migraines occur (5.3)
- Hormonally-sensitive malignancy: Discontinue FEMLYV if a hormonally-sensitive malignancy is diagnosed (5.4).
- Liver disease: Discontinue use if jaundice or acute or chronic disturbances of liver function occurs (5.5)
- Glucose tolerance and hypertriglyceridemia: Monitor glucose in females with prediabetes and diabetes taking FEMLYV. Consider an alternative contraceptive method for women with uncontrolled dyslipidemia (5.7)
- Gallbladder disease and cholestasis: Consider discontinuing FEMLYV in females with symptomatic gallbladder or cholestatic disease (5.8)
- Uterine bleeding: Evaluate irregular bleeding or amenorrhea (5.9)

6 ADVERSE REACTIONS

- The most common adverse reactions in clinical trials (≥2%) were: headache, vaginal candidiasis, nausea, menstrual cramps, breast tenderness, bacterial vaginitis, abnormal cervical smear, acne, mood swings, and weight gain. (6.1)

To report SUSPECTED ADVERSE REACTIONS, contact Millicent U.S. Inc. at 1-877-810-2101 or FDA at 1-800-FDA-1088 or www.fda.gov/medwatch.

7 DRUG INTERACTIONS

- CYP3A Inducers: May lead to contraceptive failure and/or increase breakthrough bleeding. Avoid concomitant use. If concomitant use is unavoidable, use a back-up method or alternative method of contraception during co-administration and up to 28 days after discontinuation of the CYP3A inducer (7.1)
- See Full Prescribing Information for additional clinically significant drug interactions (7)

8 USE IN SPECIFIC POPULATIONS

- Pregnancy: Discontinue if pregnancy occurs (8.1)
- Lactation: Advise postpartum females that FEMLYV can decrease milk production (8.2)

FULL PRESCRIBING INFORMATION

WARNING: CIGARETTE SMOKING AND SERIOUS CARDIOVASCULAR EVENTS

Cigarette smoking increases the risk of serious cardiovascular events from combined oral contraceptive (COC) use. This risk increases with age, particularly in females over 35 years of age, and with the number of cigarettes smoked. For this reason, COCs, including FEMLYV, are contraindicated in females who are over 35 years of age and smoke [see Contraindications (4) and Warnings & Precautions (5)].

1 INDICATIONS AND USAGE

FEMLYV is indicated for use by females of reproductive potential to prevent pregnancy [see Clinical Studies (14)].

Limitations of Use

The efficacy of FEMLYV in females with a body mass index (BMI) of more than 35 kg/m^2 has not been evaluated.

2 DOSAGE AND ADMINISTRATION

2.1 Dosing FEMLYV

To achieve maximum contraceptive effectiveness, take one ODT every day at about the same time each day. Place one ODT on the tongue, allow to disintegrate and then follow with 8 oz. (240 mL) of water. The tablets can also be swallowed whole with 8 oz. (240 mL) of water. The recommended dosage of FEMLYV is one ODT daily for 28 consecutive days: one green active ODT daily during the first 24 days followed by one white inert ODT daily during the 4 following days (see Table 1). FEMLYV must be taken in the order directed on the blister pack. ODTs should not be skipped or taken at intervals exceeding 24 hours. FEMLYV may be administered without regard to meals [see 12.3]. Instruct the patient to begin taking FEMLYV either on the first day of her menstrual period (Day 1 Start) or on the first Sunday after the onset of her menstrual period (Sunday Start).

2.2 Recommended Dosage and Administration

Table 1 FEMLYV Administration Instructions
Starting FEMLYV in females with no current use of hormonal contraception | Important:; - In females with irregular menstrual cycles, pregnancy testing may be necessary prior to initiation of this product; Day 1 Start:; - Take first green FEMLYV without regard to meals on the first day of menstruation - Take one green FEMLYV daily for 24 consecutive days, followed by one white FEMLYV daily on days 25 through to 28 - FEMLYV should be taken in the order directed on the package at the same time each day - Non-hormonal contraception (e.g. condoms and/or spermicide) should be used during the first 7 days if FEMLYV is started on a day other than the first day of menstruation
Starting FEMLYV in females with no current use of hormonal contraception | Sunday Start:; - Take one green FEMLYV daily, beginning on the first Sunday after the onset of menstruation - Take one green FEMLYV daily for 24 consecutive days, followed by one white FEMLYV daily on days 25 through to 28 - FEMLYV should be taken in the order directed on the package at the same time each day - Non-hormonal contraception should be used during the first 7 days if FEMLYV is started on a day other than the first day of menstruation - Begin next and all subsequent 28-day regimens of FEMLYV on the same day of the week as the first cycle pack (i.e., on the day after taking the last tablet)
Switching to Femlyv from another contraceptive method: | Start FEMLYV on the day:
- Combined Oral Contraceptive (COC) | Start FEMLYV on the day when the new pack of the previous COC would have been started
- Transdermal System | Start FEMLYV on the day when the next application would have been scheduled
- Vaginal insert | Start FEMLYV on the day when next insertion would have been scheduled
- Injection | Start FEMLYV on the day when next injection would have been scheduled
- Intrauterine System (IUS) | Start FEMLYV on the day of removal
- Implant | Start FEMLYV on the day of removal
- Progestin-only pill | Start FEMLYV after the last tablet was taken
Starting FEMLYV after delivery (>20 weeks gestation) | Must not start earlier than 4 weeks after delivery (due to the increased risk of thromboembolism [see Contraindications (4) and Warnings and Precautions (5.1)]; If menstrual cycles have returned, follow instructions for “Starting FEMLYV in females with no current use of hormonal contraception”. If menstrual cycles have not resumed, consider the possibility of ovulation and pregnancy. If not pregnant, use additional nonhormonal contraception for the first 7 days of FEMLYV use.
Starting FEMLYV after Abortion or Miscarriage; - ≤ 14 weeks gestation | Within the first 7 days of complete first trimester abortion or miscarriage, use additional nonhormonal contraception for the next 7 days. After the first 7 days, follow instructions for “Starting FEMLYV in females with no current use of hormonal contraception”.
- > 14 weeks but ≤ 20 weeks gestation | After 4 weeks following second trimester abortion or miscarriage. Consider duration of pregnancy and increased risk of thromboembolism [see Warnings and Precautions (5.1)] If menstrual cycles have returned, follow instructions for “Starting FEMLYV in females with no current use of hormonal contraception”. If menstrual cycles have not resumed, consider the possibility of ovulation and pregnancy. If not pregnant, use additional nonhormonal contraception for the first 7 days of FEMLYV use.

2.3 Missed Doses

Table 2. Instructions for Missed FEMLYV ODTs
If one green active ODT is missed | Take the missed ODT as soon as possible. Take the next ODT at the regular time.; Continue taking one ODT a day until the pack is finished.; Additional nonhormonal contraception (such as condoms) is not needed.
If two green active ODTs in a row are missed in Week 1 or Week 2 of the blister pack | Take the two missed ODTs as soon as possible, and the next two ODTs the next day. Continue taking one ODT a day until the pack is finished. Use additional nonhormonal contraception (such as condoms) until green ODTs have been taken for 7 consecutive days.
If two green active ODTs are missed in Week 3 or Week 4 of the blister pack | Day 1 Starter:; Discard the rest of the blister pack and start a new pack of ODTs that same day. Sunday Starter:; Keep taking one ODT every day until Sunday. On Sunday, discard the rest of the blister pack and start a new pack of ODTs that same day.
 | Use additional nonhormonal contraception (such as condoms) until green ODTs have been taken for 7 consecutive days.
If three or more green active ODTs in a row are missed | Day 1 Starter:; Discard the rest of the blister pack and start a new pack that same day. Sunday Starter:; Keep taking one ODT every day until Sunday. On Sunday, discard the rest of the blister pack and start a new blister pack of ODTs that same day.; Bleeding may occur during the week following the missed ODTs.; Use additional nonhormonal contraception (such as condoms) until green ODTs have been taken for 7 consecutive days.
If any of the four white inert ODTs are missed | Discard the missed ODTs. Continue taking the remaining ODTs until the blister pack is finished.; Additional nonhormonal contraception (such as condoms) is not needed.

2.4 Advice in Case of Gastrointestinal Disturbances

If vomiting or acute diarrhea occurs within 3 to 4 hours after taking an active ODT, take the new active ODT (scheduled for the next day) as soon as possible. If two or more active ODTs are missed, follow the advice concerning missed ODTs, including using backup non-hormonal contraception. For additional recommendations, refer to the table above [see Dosage and Administration (2.3)].

3 DOSAGE FORMS AND STRENGTHS

Orally disintegrating tablets:

- 1 mg norethindrone acetate and 0.02 mg ethinyl estradiol, green, round ODTs, imprinted with “M” on one side and “312” on the other side
- White, round, inert ODTs imprinted with “M” on one side and “313” on the other side

4 CONTRAINDICATIONS

FEMLYV is contraindicated in females who are known to have or develop the following conditions:

- A history of, increased risk for, or current arterial or venous thrombotic/thromboembolic diseases.

Examples include women who are known to:

- Smoke, if 35 years of age and older [see Boxed Warning and Warnings and Precautions (5.1)]
- Have current or history of deep vein thrombosis or pulmonary embolism [see Warnings and Precautions (5.1)]
- Have cerebrovascular disease [see Warnings and Precautions (5.1)]
- Have coronary artery disease [see Warnings and Precautions (5.1)]
- Have thrombogenic valvular or thrombogenic rhythm diseases of the heart (for example, subacute bacterial endocarditis with valvular disease, or atrial fibrillation) [see Warnings and Precautions (5.1)]
- Have inherited or acquired hypercoagulopathies [see Warnings and Precautions (5.1)]
- Have uncontrolled hypertension or hypertension with vascular disease [see Warnings and Precautions (5.2)]
- Have diabetes mellitus with hypertension or end-organ damage; or diabetes mellitus of > 20 years duration [see Warnings and Precautions (5.7)]
- Have migraine headaches with aura
  - All women over age 35 with migraine headache [see Warnings and Precautions (5.3)]
- Current diagnosis of, or history of, breast cancer, which may be hormone-sensitive [see Warnings and Precautions (5.4)]
- Liver tumors, benign or malignant, or hepatic impairment [see Warnings and Precautions (5.5)]
- Use of Hepatitis C drug combinations containing ombitasvir/paritaprevir/ritonavir, with or without dasabuvir, due to the potential for ALT elevations [see Warnings and Precautions (5.6)]
- Undiagnosed abnormal uterine bleeding [see Warnings and Precautions (5.9)]

5 WARNINGS AND PRECAUTIONS

5.1 Thromboembolic Disorders and Other Vascular Problems

Stop FEMLYV if an arterial or deep venous thrombotic event (VTE) occurs.

Stop FEMLYV if there is unexplained loss of vision, proptosis, diplopia, papilledema, or retinal vascular lesions and evaluate for retinal vein thrombosis immediately.

Discontinue FEMLYV during prolonged immobilization.

If feasible, discontinue FEMLYV at least 4 weeks before and through 2 weeks after major surgery or other surgeries known to have an elevated risk of VTE.

Start FEMLYV no earlier than 4 weeks after delivery in females who are not breastfeeding. The risk of postpartum thromboembolism decreases after the third postpartum week, whereas the likelihood of ovulation increases after the third postpartum week.

Before starting FEMLYV, evaluate any past medical history or family history of thrombotic or thromboembolic disorders and consider whether the history suggests an inherited or acquired hypercoagulopathy. FEMLYV is contraindicated in females with a high risk of arterial or venous thrombotic/thromboembolic diseases [see Contraindications (4)].

Cardiovascular and Cerebrovascular Events

Use of CHCs increases the risk of cardiovascular events and cerebrovascular events, such as myocardial infarction and stroke. The risk is greater among females over age 40, smokers, and females with hypertension, dyslipidemia, diabetes, or obesity. The risk increases with age, particularly in females 35 years of age and older, and with the number of cigarettes smoked. In addition to cigarettes, use of other nicotine-containing products – including cigars, smokeless tobacco, hookah tobacco, e-cigarettes, and nicotine replacement therapy – may also increase the risk of serious cardiovascular events from CHC use.

Venous Thromboembolism

Use of CHCs also increases the risk of venous thromboembolic events (VTEs), such as deep vein thrombosis and pulmonary embolism. The rate of VTE in females using COCs has been estimated to be 3 to 9 cases per 10,000 woman-years and should be considered in the context of other female of reproductive potential subpopulations who are not taking CHCs [see Adverse Reactions (6.1)].

Risk factors for VTEs include smoking, obesity, family history of VTE, and prolonged immobilization in addition to other factors that contraindicate use of CHCs [see Contraindications (4)]. The presence of multiple risk factors for VTE may increase the risk synergistically. The risk of VTE is highest during the first year of CHC use and when restarting hormonal contraception after a break of four weeks or longer. The risk of VTE returns to baseline approximately 3 months after CHC use is discontinued.

Postpartum Venous Thromboembolism

The risk of VTE is increased during the first six weeks postpartum compared to the risk in nonpregnant, non-postpartum females. The risk is highest in the first three weeks postpartum but remains higher than baseline until at least six weeks postpartum. The presence of multiple risk factors for VTE may further increase the risk. Obstetric complications may extend the elevated risk up to 12 weeks postpartum.

Figure 1 shows the risk of developing a VTE for females who are not pregnant and do not use COCs, for females who use COCs, for pregnant females, and for females in the postpartum period. To put the risk of developing a VTE into perspective: if 10,000 females who are not pregnant and do not use oral contraceptives are followed for one year, between 1 and 5 of these females will develop a VTE.

Figure 1 Likelihood of Developing a VTE

5.2 High Blood Pressure

FEMLYV is contraindicated in females with uncontrolled hypertension or hypertension with vascular disease [see Contraindications (4)]. For all females, including those with well-controlled hypertension, monitor blood pressure and stop FEMLYV if blood pressure rises significantly.

An increase in blood pressure has been reported in females taking CHCs, and this increase is more likely in older women with extended duration of use.

5.3 Migraine

FEMLYV is contraindicated in females who have migraines with aura [see Contraindications (4)]. Discontinue FEMLYV in females using FEMLYV who develop new migraines that are recurrent, persistent, or severe. Discontinue FEMLYV if there is an increased frequency or severity of migraines during CHC use (which may be prodromal of a cerebrovascular event).

Migraines with aura increase the risk for stroke. This stroke risk is further increased in females who have migraines with aura with use of CHCs.

5.4 Malignant Neoplasms

Breast Cancer

FEMLYV is contraindicated in females who currently have or have had breast cancer because breast cancer may be hormonally sensitive [see Contraindications (4)].

Epidemiology studies have not found a consistent association between use of combined oral contraceptives (COCs) and breast cancer risk. Studies do not show an association between ever (current or past) use of COCs and risk of breast cancer. However, some studies report a small increase in the risk of breast cancer among current or recent users (<6 months since last use) and current users with longer duration of COC use [see Postmarketing Experience (6.2)].

Cervical Cancer

A causal relationship between the use of CHCs and the development of cervical cancer and intraepithelial neoplasia has not been clearly established. In observational studies, the use of oral hormonal contraceptives in females for five years or more, compared to females who did not use oral hormonal contraceptives, was associated with an increased risk of cervical cancer and intraepithelial neoplasia. In these studies, the use of oral hormonal contraceptives in females for 10 years or more, compared to females who received oral hormonal contraceptives for 5-9 years, was associated with an increased risk of cervical cancer and intraepithelial neoplasia. Limitations in these epidemiologic studies include potential recall bias, differences in sexual behavior, and other factors such as establishing whether there were data on persistent high-risk Human Papilloma Virus (HPV) infection.

5.5 Liver Disease

Elevated Liver Enzymes

FEMLYV is contraindicated in females with acute hepatitis or severe (decompensated) cirrhosis of the liver [see Contraindications (4)]. Withhold or permanently discontinue FEMLYV for persistent or significant elevation of liver enzymes. FEMLYV can cause elevated liver enzymes. Discontinue FEMLYV if jaundice develops.

Liver Tumors

FEMLYV is contraindicated in females with hepatic adenomas and malignant liver tumors [see Contraindications (4)]. CHCs increase the risk of hepatic tumors, particularly, hepatic adenomas. Rupture of hepatic adenomas may cause death from abdominal hemorrhage.

5.6 Risk of Liver Enzyme Elevations with Concomitant Hepatitis C Treatment

CHCs, such as FEMLYV, are contraindicated for use with Hepatitis C drug combinations containing ombitasvir/paritaprevir/ritonavir (with or without dasabuvir) [see Contraindications (4)]. Discontinue FEMLYV prior to starting therapy with the combination drug regimen ombitasvir/paritaprevir/ritonavir (with or without dasabuvir). FEMLYV can be restarted approximately 2 weeks following completion of treatment with this hepatitis C combination drug regimen.

During clinical trials with the above-mentioned Hepatitis C combination drug regimen, ALT elevations greater than 5 times the upper limit of normal (ULN), including some cases greater than 20 times the ULN, were significantly more frequent in females using ethinyl estradiol (EE)-containing drugs, such as CHCs.

5.7 Glucose Tolerance and Hypertriglyceridemia

Glucose Tolerance

Carefully monitor females with prediabetes and diabetes who are using FEMLYV. FEMLYV may decrease glucose tolerance.

Hypertriglyceridemia

Consider alternative contraception for females with hypertriglyceridemia. Females with hypertriglyceridemia, or a family history thereof, may have an increase in serum triglyceride concentrations when using FEMLYV, which may increase the risk of pancreatitis.

5.8 Gallbladder Disease and Cholestasis

Consider discontinuing FEMLYV in females with symptomatic gallbladder disease or cholestatic disease. Studies suggest an increased risk of developing gallbladder disease among CHC users. Use of CHCs may also worsen existing gallbladder disease.

A past history of CHC-related cholestasis predicts an increased risk with subsequent CHC use. Women with a history of pregnancy-related cholestasis may be at an increased risk for CHC-related cholestasis.

5.9 Bleeding Irregularities and Amenorrhea

Unscheduled Bleeding and Spotting

Females using FEMLYV may experience unscheduled (breakthrough or intracyclic) bleeding and spotting, especially during the first three months of use. Bleeding irregularities may resolve over time or by changing to a different contraceptive product. If bleeding persists or occurs after previously regular cycles, evaluate for causes such as pregnancy or malignancy.

Based on patient diaries from a clinical trial evaluating the safety and efficacy of a 24-day regimen of norethindrone acetate 1 mg/ethinyl estradiol 0.020 mg tablets, 24-35% of women experienced unscheduled bleeding per cycle. A total of 10 subjects out of 743 (1.3%) discontinued due to bleeding or spotting [see Adverse Reactions (6.1)].

Amenorrhea and Oligomenorrhea

If scheduled (withdrawal) bleeding does not occur, consider the possibility of pregnancy. If the patient has not adhered to the prescribed dosing schedule (missed one or more active tablets or started taking them on a day later than she should have), consider the possibility of pregnancy at the time of the first missed period and take appropriate diagnostic measures. If the patient has adhered to the prescribed regimen and misses two consecutive periods, rule out pregnancy.

Females who use FEMLVY may experience absence of scheduled (withdrawal) bleeding, even if they are not pregnant. In the clinical trial with a 24-day regimen of norethindrone acetate 1 mg/ethinyl estradiol 0.020 mg tablets, 22 to 36% of the women using norethindrone acetate 1 mg/ethinyl estradiol 0.020 mg tablets experienced amenorrhea in at least one of 6 cycles of use [see Adverse Reactions (6.1)].

After discontinuation of FEMLYV, amenorrhea or oligomenorrhea may occur, especially if these conditions were pre-existent.

5.10 Depression

Monitor females with a history of depression and discontinue FEMLYV if depression recurs to a serious degree. Data on the association of COCs with onset of depression or exacerbation of existing depression are limited.

5.11 Effect on Binding Globulins

Increase the dosage of thyroid hormone replacement therapy as needed in females taking FEMLYV [see Clinical Pharmacology (12.2)]. The estrogen component of FEMLYV may increase the serum concentrations of thyroxine-binding globulin, sex hormone-binding globulin, and cortisol-binding globulin.

5.12 Hereditary Angioedema

Avoid FEMLYV in females with hereditary angioedema. Exogenous estrogens may induce or exacerbate symptoms of hereditary angioedema.

5.13 Chloasma

Avoid FEMLYV in females with a history of chloasma gravidarum or increased sensitivity to sun and/or ultraviolet radiation exposure. Chloasma may occur with FEMLYV, especially in females with a history of chloasma gravidarum.

6 ADVERSE REACTIONS

The following serious adverse reactions with the use of COCs are discussed elsewhere in the labeling:

- Serious cardiovascular events and stroke [see Boxed Warning and Warnings and Precautions (5.1)]
- Vascular events [see Warnings and Precautions (5.1)]
- Liver disease [see Warnings and Precautions (5.5)]

6.1 Clinical Trial Experience

Because clinical trials are conducted under widely varying conditions, adverse reaction rates observed in the clinical trials of a drug cannot be directly compared to the rates in the clinical trials of another drug and may not reflect the rates observed in practice.

The safety of FEMLYV has been established from adequate and well-controlled studies of norethindrone acetate 1 mg/ethinyl estradiol 0.020 mg tablets in adult females of reproductive potential for the prevention of pregnancy [see Clinical Studies (14)]. The data described below reflect exposure to norethindrone acetate 1 mg/ethinyl estradiol 0.020 mg tablets.

Common Adverse Reactions (Greater Than or Equal to 2% of all Treated Subjects): The most common adverse reactions reported by at least 2% of the 743 women using norethindrone acetate/ethinyl estradiol tablets were the following, in order of decreasing incidence: headache (6.3%), vaginal candidiasis (6.1%), nausea (4.6%), menstrual cramps (4.4%), breast tenderness (3.4%), bacterial vaginitis (3.1%), abnormal cervical smear (3.1%), acne (2.7%), mood swings (2.2%), and weight gain (2.0%).

Adverse Reactions Leading to Study Discontinuation: Among the 743 women using norethindrone acetate/ethinyl estradiol tablets, 46 women (6.2%) withdrew because of an adverse event. Adverse events occurring in 3 or more subjects leading to discontinuation of treatment were, in decreasing order: abnormal or irregular bleeding (1.3%), nausea (0.8%), menstrual cramps (0.5%), and increased blood pressure (0.4%).

6.2 Postmarketing Experience

Five studies that compared breast cancer risk between ever-users (current or past use) of COCs and never-users of COCs reported no association between ever use of COCs and breast cancer risk, with effect estimates ranging from 0.90 - 1.12 (Figure 2).

Three studies compared breast cancer risk between current or recent COC users (<6 months since last use) and never users of COCs (Figure 1). One of these studies reported no association between breast cancer risk and COC use. The other two studies found an increased relative risk of 1.19 - 1.33 with current or recent use. Both of these studies found an increased risk of breast cancer with current use of longer duration, with relative risks ranging from 1.03 with less than one year of COC use to approximately 1.4 with more than 8-10 years of COC use.

Figure 2.

RR = relative risk; OR = odds ratio; HR = hazard ratio. “ever COC” are females with current or past COC use; “never COC use” are females that never used COCs.

The following adverse reactions have been identified during post approval use of a 24-day regimen of norethindrone acetate 1 mg/ethinyl estradiol 0.020 mg tablets. Because these reactions are reported voluntarily from a population of uncertain size, it is not always possible to reliably estimate their frequency or evaluate a causal relationship to drug exposure.

Adverse reactions are grouped into System Organ Classes.

Vascular disorders: thrombosis/embolism (coronary artery, pulmonary, cerebral, deep vein).

Hepatobiliary disorders: cholelithiasis, cholecystitis, hepatic adenoma, hemangioma of liver.

Immune system disorders: hypersensitivity reaction.

Skin and subcutaneous disorders: alopecia, rash (generalized and allergic), pruritus, skin discoloration.

GI disorders: nausea, vomiting, abdominal pain.

Musculoskeletal and connective tissue disorders: myalgia.

Eye disorders: blurred vision, visual impairment, corneal thinning, change in corneal curvature (steepening).

Infections and infestations: fungal infection, vaginal infection.

Investigations: change in weight or appetite (increase or decrease), fatigue, malaise, peripheral edema, blood pressure increased.

Nervous system disorders: headache, dizziness, migraine, loss of consciousness.

Psychiatric disorders: mood swings, depression, insomnia, anxiety, suicidal ideation, panic attack, changes in libido.

Renal and urinary disorders: cystitis-like syndrome.

Reproductive system and breast disorders: breast changes (tenderness, pain, enlargement, and secretion), premenstrual syndrome, dysmenorrhea.

Cardiovascular: chest pain, palpitations, tachycardia, myocardial infarction.

7 DRUG INTERACTIONS

7.1 Effects of Other Drugs on Combined Oral Contraceptives

Substances diminishing the efficacy of COCs: Drugs or herbal products that induce certain enzymes, including cytochrome P450 3A4 (CYP3A4), may decrease the effectiveness of COCs or increase breakthrough bleeding. Some drugs or herbal products that may decrease the effectiveness of hormonal contraceptives include phenytoin, barbiturates, carbamazepine, bosentan, felbamate, griseofulvin, oxcarbazepine, rifampicin, topiramate and products containing St. John’s wort. Interactions between oral contraceptives and other drugs may lead to breakthrough bleeding and/or contraceptive failure. Counsel women to use an alternative method of contraception or a back-up method when enzyme inducers are used with COCs, and to continue back-up contraception for 28 days after discontinuing the enzyme inducer to ensure contraceptive reliability.

Substances increasing the plasma concentrations of COCs: Co-administration of atorvastatin and certain COCs containing ethinyl estradiol increase AUC values for ethinyl estradiol by approximately 20%. Ascorbic acid and acetaminophen may increase plasma ethinyl estradiol concentrations, possibly by inhibition of conjugation. CYP3A4 inhibitors such as itraconazole or ketoconazole may increase plasma hormone concentrations.

Human immunodeficiency virus (HIV)/ Hepatitis C virus (HCV) protease inhibitors and non- nucleoside reverse transcriptase inhibitors: Significant changes (increase or decrease) in the plasma concentrations of the estrogen and progestin have been noted in some cases of co-administration of HIV/HCV protease inhibitors or of non-nucleoside reverse transcriptase inhibitors.

Antibiotics: There have been reports of pregnancy while taking hormonal contraceptives and antibiotics, but clinical pharmacokinetic studies have not shown consistent effects of antibiotics on plasma concentrations of synthetic steroids.

7.2 Effects of Combined Oral Contraceptives on Other Drugs

COCs containing ethinyl estradiol may inhibit the metabolism of other compounds. COCs have been shown to significantly decrease plasma concentrations of lamotrigine, likely due to induction of lamotrigine glucuronidation. This may reduce seizure control; therefore, dosage adjustments of lamotrigine may be necessary.

Women on thyroid hormone replacement therapy may need increased doses of thyroid hormone because serum concentration of thyroid-binding globulin increases with use of COCs.

7.3 Concomitant Use with HCV Combination Therapy – Liver Enzyme Elevation

Do not co-administer FEMLYV with HCV drug combinations containing ombitasvir/paritaprevir/ritonavir, with or without dasabuvir, due to potential for ALT elevations [see Warnings and Precautions (5.6)].

7.4 Interference with Laboratory Tests

The use of contraceptive steroids may influence the results of certain laboratory tests, such as coagulation factors, lipids, glucose tolerance, and binding proteins.

8 USE IN SPECIFIC POPULATIONS

8.1 Pregnancy

Risk Summary

Discontinue FEMLYV if pregnancy occurs, because there is no reason to use hormonal contraceptives during pregnancy. Epidemiologic studies and meta-analyses have not found an increased risk of genital or nongenital birth defects (including cardiac anomalies and limb-reduction defects) following exposure to COCs before conception or during early pregnancy.

In the U.S. general population, the estimated background risk of major birth defects and miscarriage in clinically recognized pregnancies is 2 to 4 percent and 15 to 20 percent, respectively.

8.2 Lactation

Risk Summary

Contraceptive hormones and/or metabolites are present in human milk. COCs can reduce milk production in breast-feeding females. This reduction can occur at any time but is less likely to occur once breast-feeding is well-established. When possible, advise the nursing female to use other methods of contraception until she discontinues breast-feeding [see Dosage and Administration (2.2)]. The developmental and health benefits of breast-feeding should be considered along with the mother’s clinical need for FEMLYV and any potential adverse effects on the breast-fed child from FEMLYV or from the underlying maternal condition.

8.4 Pediatric Use

Safety and efficacy of FEMLYV have been established in females of reproductive potential. Efficacy is expected to be the same in postmenarcheal adolescents younger than 17 years as for users 17 years and older. FEMLYV is not indicated before menarche.

8.7 Hepatic Impairment

FEMLYV is contraindicated in females with hepatic impairment [see Contraindications (4), Warnings and Precautions (5.5)]. Steroid hormones may be poorly metabolized in patients with hepatic impairment. Acute or chronic disturbances of liver function may necessitate the discontinuation of COC use until markers of liver function return to normal and COC causation has been excluded [see Contraindications (4) and Warnings and Precautions (5.5)].

8.8 Body Mass Index

The safety and effectiveness of FEMLYV in females with a BMI greater than 35 kg/m^2 have not been fully evaluated [see Clinical Studies (14)].

10 OVERDOSAGE

Overdosage of CHCs may cause nausea, vomiting, and severe headaches. Individual reports of thromboembolic complications and vaginal bleeding have occurred from overdosage. Pediatric patients with unintended CHC ingestion have reported nausea and vomiting and some developed irritability and drowsiness; rare reports described vaginal bleeding.

Overdosage Management Recommendations

Consider short-term prophylactic anticoagulation therapy for patients with high risk of VTE.

11 DESCRIPTION

FEMLYV (norethindrone acetate and ethinyl estradiol orally disintegrating tablets) is a combined oral contraceptive. FEMLYV consists of 24 green, round ODTs each containing 1 mg norethindrone acetate and 0.020 mg ethinyl estradiol and 4 white, round inert ODTs.

Each green ODT also contains the following inactive ingredients: croscarmellose sodium, magnesium stearate, mannitol, microcrystalline cellulose, mint green lake blend, pregelatinized starch, spearmint flavor, sucralose, vitamin E (DL-alpha-tocopherol).

Each white ODT contains, croscarmellose sodium, magnesium stearate, mannitol, microcrystalline cellulose, pregelatinized starch, spearmint flavor, sucralose.

The empirical formula of norethindrone acetate is C22H28O3 and the structural formula is:

The chemical name of norethindrone acetate is [19-Norpregn-4-en-20-yn-3-one, 17-(acetyloxy)-, (17α)-]. The molecular weight of norethindrone acetate is 340.46. It is a neutral molecule and is practically insoluble in water.

The empirical formula of ethinyl estradiol is C20H24O2 and the structural formula is:

The chemical name of ethinyl estradiol is [19-Norpregna-1,3,5(10)-trien-20-yne-3,17-diol, (17α)-]. The molecular weight of ethinyl estradiol is 296.40. It is a neutral molecule and is practically insoluble in water.

12 CLINICAL PHARMACOLOGY

12.1 Mechanism of Action

CHCs lower the risk of becoming pregnant primarily by suppressing ovulation.

12.2 Pharmacodynamics

No specific pharmacodynamic studies were conducted with FEMLYV.

12.3 Pharmacokinetics

Absorption

Norethindrone acetate appears to be completely and rapidly deacetylated to norethindrone after oral administration The absolute bioavailability was approximately 64% for norethindrone and 43% for ethinyl estradiol following oral administration.

The plasma norethindrone and ethinyl estradiol pharmacokinetics following single-dose administrations of FEMLYV ODT in 36 healthy female subjects are provided in Figures 3 and 4, and Table 3.

Figure 3. Mean (± Standard Deviation) Plasma Norethindrone Concentration-Time Profile Following Single-Dose Administration of FEMLYV ODT to Healthy Female Volunteers under Fasting Conditions (n = 36)
Figure 4. Mean (± Standard Deviation) Plasma Ethinyl Estradiol Concentration- Time Profile Following Single-Dose Administration of FEMLYV ODT to Healthy Female Volunteers under Fasting Conditions (n = 36)

Table 3. Summary of Norethindrone (NE) and Ethinyl Estradiol (EE) Pharmacokinetics Following Single-Dose Administration of FEMLYV ODT to Healthy Female Volunteers Under Fasting Conditions (n = 36)
Analyte | Arithmetic Meana (% CV) by Pharmacokinetic Parameter
Analyte | Cmax (pg/mL) | tmax (hr) | AUC(0-tldc) (pg•h/mL) | AUC(0-inf) (pg•h/mL) | t½ (hr)
NE | 8438; (34) | 1.33; (0.66–2.50) | 50060; (48) | 51190; (49) | 10.25; (26)
EE | 62.8; (25) | 1.33; (0.67–2.03) | 505.1; (25) | 595.6b; (24) | 18.02b; (34)
Cmax = Maximum plasma concentration
tmax = Time of Cmax
AUC(0-tldc) = Area under plasma concentration versus time curve from 0 to tldc, the time of last determinable concentration
AUC(0-inf) = Area under the plasma concentration versus time curve from time 0 to infinity
t½ = Terminal phase half-life
% CV = Coefficient of Variation (%)
a The median (range) is reported for tmax
b n = 35

Effect of Food

No clinically significant differences in pharmacokinetics of norethindrone and ethinyl estradiol were observed following administration of a high-fat meal in healthy premenopausal subjects.

Distribution

Volume of distribution of norethindrone and ethinyl estradiol ranges from 2 to 4 L/kg. Plasma protein binding of both steroids is extensive (greater than 95%); norethindrone binds to both albumin and SHBG, whereas ethinyl estradiol binds only to albumin. Although ethinyl estradiol does not bind to SHBG, it induces SHBG synthesis.

Metabolism

Norethindrone undergoes extensive biotransformation, primarily via reduction, followed by sulfate and glucuronide conjugation. The majority of metabolites in the circulation are sulfates, with glucuronides accounting for most of the urinary metabolites.

Ethinyl estradiol is also extensively metabolized, both by oxidation and by conjugation with sulfate and glucuronide. Sulfates are the major circulating conjugates of ethinyl estradiol and glucuronides predominate in urine. The primary oxidative metabolite is 2-hydroxy ethinyl estradiol, formed by the CYP3A4 isoform of cytochrome P450. Part of the first-pass metabolism of ethinyl estradiol is believed to occur in gastrointestinal mucosa. Ethinyl estradiol may undergo enterohepatic circulation.

Excretion

Norethindrone and ethinyl estradiol are excreted in both urine and feces, primarily as metabolites. Plasma clearance values for norethindrone and ethinyl estradiol are similar (approximately 0.4 L/hr/kg). Elimination half-lives of norethindrone and ethinyl estradiol following administration of FEMLYV are approximately 10 hours and 18 hours, respectively.

13 NONCLINICAL TOXICOLOGY

13.1 Carcinogenesis, Mutagenesis, Impairment of Fertility

[See Warnings and Precautions (5.4, 5.5)].

14 CLINICAL STUDIES

The effectiveness of FEMLYV has been established for the prevention of pregnancy in females of reproductive potential based on adequate and well-controlled studies of norethindrone acetate/ethinyl estradiol tablets. The data presented below reflects results from studies of norethindrone acetate/ethinyl estradiol tablets.

In a clinical study, 743 women 18 to 45 years of age were studied to assess the efficacy of norethindrone acetate/ethinyl estradiol tablets, for up to six 28-day cycles providing a total of 3,823 treatment-cycles of exposure. The racial demographic of all enrolled women was: 70% Caucasian, 16% African American, 10% Hispanic, 2% Asian and 2% Other. Women with BMI greater than 35 kg/m^2 were excluded from the study. The weight range for those women treated was 90 to 260 pounds, with a mean weight of 147 pounds. Among the women in the study, about 40% had not used hormonal contraception immediately prior to enrolling in this study.

A total of 583 women completed 6 cycles of treatment. There were a total of 5 on-treatment pregnancies in 3,565 treatment cycles during which no backup contraception was used. The Pearl Index for norethindrone acetate and ethinyl estradiol tablets was 1.82 (95% confidence interval 0.59 - 4.25).

16 HOW SUPPLIED/STORAGE AND HANDLING

16.1 How Supplied

FEMLYV (norethindrone acetate and ethinyl estradiol orally disintegrating tablets), 1 mg/0.02 mg is available in a carton of three pouches, each pouch contains a blister card of 28 ODTs.

Each blister card contains 28 ODTs in the following order:

- 24 green, round active ODTs imprinted with “M” on one side and “312” on the other side.
- 4 white, round inert ODTs imprinted with “M” on one side and “313” on the other side.

NDC 72495-601-84, cartons of 3 pouches, each pouch contains a blister card of 28 ODTs.

NDC 72495-601-28, cartons of 1 pouch, each pouch contains a blister card of 28 ODTs.

16.2 Storage Conditions

Store at 20°C to 25º C (68°F to 77º F); excursions permitted to 15°C to 30º C (59°F to 86º F) [See USP Controlled Room Temperature].

16.3 Disposal

Dispose unused medication via a take-back option if available. Otherwise, follow FDA instructions for disposing medication in the household trash, www.fda.gov/drugdisposal. Do NOT flush down the toilet.

17 PATIENT COUNSELING INFORMATION

Advise the patient to read the FDA-Approved patient labeling (Patient Information)

Sexually Transmitted Infections

Advise females that FEMLYV does not protect against HIV infection or other sexually transmitted infections.

Important Administration Instructions and Instructions for Missed Doses

Instruct females to take one FEMLYV orally once at the same time every day by allowing the FEMLYV to disintegrate on the tongue or swallowing whole, then follow with 8 oz (240 mL) of water. Advise patients about what to do in the event that ODTs are missed [see Dosage and Administration (2)].

- Advise females starting FEMLYV to use additional nonhormonal contraception for 7 days after the first dose unless FEMLYV is started on the first day (Day 1) of menses [see Dosage and Administration (2)]
- Advise females who miss more than two consecutive days of FEMLYV or experience vomiting or diarrhea for > 48 hours consecutively to use additional nonhormonal contraception for 7 days [see Dosage and Administration (2.3, 2.4)]

Thromboembolic Disorders and Other Vascular Problems [see Warnings and Precautions (5.1)].

- Advise females that there is an increased risk of arterial and/or venous thrombotic/thromboembolic events with FEMLYV and the risk of arterial and/or venous thrombotic/thromboembolism is greater in smokers and females with preexisting medical conditions including hypertension, dyslipidemia, diabetes, and obesity.
- Advise patients of the pertinent factors that further increase their risk and ways to diminish the risk, e.g., to stop smoking (if applicable)
- Advise patients to contact their healthcare professional for any signs or symptoms of arterial and/or VTE
- Advise patients to contact their healthcare professional if they will be immobilized for a prolonged period of time

Hypertension

Advise females that FEMLYV can cause an increase in blood pressure over time. Instruct patients to contact their healthcare professional if blood pressure increases [see Warnings and Precautions (5.2)].

Liver Disease

Advise females that use of FEMLYV can cause elevated liver enzymes and can increase the risk of liver tumors. Instruct females to contact their healthcare professional for any signs or symptoms of liver disease [see Warnings and Precautions (5.5)].

Glucose Tolerance

Advise females that FEMLYV may decrease glucose tolerance. Instruct females with diabetes and prediabetes to contact their healthcare professional for any signs or symptoms of hyperglycemia [see Warnings and Precautions (5.7) and Clinical Pharmacology (12.2)].

Gallbladder Disease and Cholestasis

Advise females that use of FEMLYV is associated with an increased risk of developing and/or worsening gallbladder disease. Instruct patients to contact their healthcare professional for any signs or symptoms of gallbladder disease [see Warnings and Precautions (5.8)].

Bleeding Irregularities, Amenorrhea, and Pregnancy

Advise females that FEMLYV can cause unscheduled bleeding and spotting, as well as amenorrhea and oligomenorrhea. Advise females to contact their health care professional if amenorrhea occurs in two or more consecutive cycles or symptoms of pregnancy occur, e.g., morning sickness or unusual breast tenderness. Instruct females to stop FEMLYV if pregnancy is confirmed during use [see Warnings and Precautions (5.9) and Use in Specific Populations (8.1)].

Chloasma

Advise females that FEMLYV can cause chloasma and the risk is highest in females with a history of chloasma, especially chloasma gravidarum. Instruct females to take precautions to limit UVA and UVB exposure while using FEMLYV [see Warnings and Precautions (5.13)].

Lactation

Advise postpartum females that FEMLYV may reduce breast milk production. Advise females that this reduction is less likely to occur if breast-feeding is well established [see Use in Specific Populations (8.2)].

Drug Interactions

FEMLYV may interact with many drugs, foods, and dietary supplements. Therefore, advise females to report to their healthcare professional the use of any other prescription or nonprescription drugs or dietary supplements [see Drug Interactions (7.1, 7.2)].

Distributed by:
Millicent U.S., Inc.
East Hanover, NJ 07936

© 2025 Millicent. All rights reserved.
FEMLYV and its design are trademarks of Millicent Puerto Rico LLC.

FDA-Approved Patient Labeling

Guide for Using FEMLYV

WARNING TO WOMEN WHO SMOKE

Do not use FEMLYV if you smoke cigarettes and are over 35 years old. Smoking increases your risk of serious cardiovascular side effects (heart and blood vessel problems) from birth control pills, including death from heart attack, blood clots or stroke. This risk increases with age and the number of cigarettes you smoke.

Birth control pills help to lower the chances of becoming pregnant when taken as directed. They do not protect against HIV infection (AIDS) and other sexually transmitted infections.

What is FEMLYV?

FEMLYV is a birth control pill. It contains two female hormones, an estrogen called ethinyl estradiol, and a progestin called norethindrone acetate.

How well does FEMLYV work?

Your chance of getting pregnant depends on how well you follow the directions for taking your birth control pills. The better you follow the directions, the less chance you have of getting pregnant.

Based on the results of one clinical study of a 24-day regimen of norethindrone acetate 1 mg/ethinyl estradiol 0.020 mg tablets lasting 6 months, about 1 to 4 out of 100 women may get pregnant during the first year they use FEMLYV. Women with a BMI above 35 kg/m^2 were not studied in the clinical trial, so it is not known how well FEMLYV protects against pregnancy in such women. If you are overweight, discuss with your healthcare provider whether FEMLYV is the best choice for you.

The following chart shows the chance of getting pregnant for women who use different methods of birth control. Each box on the chart contains a list of birth control methods that are similar in effectiveness. The most effective methods are at the top of the chart. The box on the bottom of the chart shows the chance of getting pregnant for women who do not use birth control and are trying to get pregnant.

How do I take FEMLYV?

1. Be sure to read these directions before you start taking your tablets or anytime you are not sure what to do.
2. The tablets should be placed on the tongue, allowed to dissolve, and followed by water or swallowed whole with water.
3. The right way to take the tablet is to take 1 tablet every day at the same time in the order directed on the package. FEMLYV can be taken with or without meals.
  If you miss tablets you could get pregnant. This includes starting the pack late. The more tablets you miss, the more likely you are to get pregnant. See the "What to Do if You Miss Tablets” section below.
4. Many women have spotting or light bleeding at unexpected times, or may feel sick to their stomach during the first 1 to 3 packs of tablets.
  If you do have spotting or light bleeding or feel sick to your stomach, do not stop taking the tablets. The problem will usually go away. If it does not go away, check with your healthcare provider.
5. Missing tablets can also cause spotting or light bleeding, even when you make up these missed tablets.
  On the days you take 2 tablets, to make up for missed tablets, you could also feel a little sick to your stomach.
6. If you have vomiting (within 3 to 4 hours after you take your tablet), you should follow the instructions for "What to Do if You Miss Tablets". If you have diarrhea or if you take certain medicines, including some antibiotics and some herbal products such as St. John's Wort, your tablets may not work as well.
  Use a back-up method (such as condoms and spermicides) until you check with your healthcare provider.
7. If you have trouble remembering to take FEMLYV, talk to your healthcare provider about how to make tablet-taking easier or about using another method of birth control.
8. If you have any questions or are unsure about the information in this leaflet, call your healthcare provider.

Before You Start Taking Your FEMLYV Tablets

1. Decide What Time of Day You Want to Take Your Tablet. It is important to take FEMLYV tablets in the order directed on the package at the same time every day. FEMLYV can be taken with or without meals.
2. The FEMLYV pack has 28 Tablets
  The FEMLYV pack has 24 active green tablets (with hormones) to be taken for 24 days, followed by 4 reminder white tablets (without hormones) to be taken for the next four days.
3. Also look for:
  a) Where on the pack to start taking tablets,
  b) In what order to take the tablets (follow the arrows shown in the picture above)
  c) The week numbers as shown in the picture above.
4. Be sure you have ready at all times
  a) another kind of birth control (such as a condoms and spermicide) to use as a back-up in case you miss tablets, and
  b) an extra, full tablet pack.

When to Start the First Pack of Tablets

You have a choice for which day to start taking your first pack of tablets. Decide with your healthcare provider which is the best day for you. Pick a time of day which will be easy to remember.

Day 1 Start:

1. Pick the day label strip that starts with the first day of your period (this is the day you start bleeding or spotting, even if it is almost midnight when the bleeding begins).
2. Place this day label strip on the tablet dispenser over the area that has the days of the week (starting with Sunday) printed on the plastic.
3. Take the first green tablet of the pack during the first 24 hours of your period.
4. You will not need to use a back-up method of birth control, since you are starting the tablet at the beginning of your period. However, if you start FEMLYV later than the first day of your period, you should use another method of birth control (such as a condom and spermicide) as a back-up method until you have taken 7 green tablets.

Sunday Start:

1. Take the first green tablet of the pack on the Sunday after your period starts, even if you are still bleeding. If your period begins on Sunday, start the pack that same day.
2. Use another method of birth control (such as a condom and spermicide) as a back-up method if you have sex anytime from the Sunday you start your first pack until the next Sunday (7 days). This also applies if you start FEMLYV after having been pregnant, and you have not had a period since your pregnancy.

When You Switch From a Different Birth Control Tablet or Capsule

When switching from another birth control pill, finish all the tablets or capsules, then FEMLYV should be started on the same day that a new pack of the previous birth control tablet or capsule would have been started.

When You Switch From Another Type of Birth Control Method

When switching from a transdermal system or vaginal insert, finish the 21 days of use, wait 7 days, then FEMLYV should be started when the next application would have been due. When switching from an injection, FEMLYV should be started when the next injection would have been due. When switching from an intrauterine device or an implant, FEMLYV should be started on the day of removal.

What to Do During the Month

1. Take 1 tablet at the same time every day until the pack is empty.
  Do not skip tablets even if you are spotting or bleeding between monthly periods or feel sick to your stomach (nausea).
2. Do not skip tablets even if you do not have sex very often.
  When you finish a pack of tablets, start the next pack on the day after your last white tablet. Do not wait any days between packs.

What to Do if You Miss Tablets

FEMLYV may not be as effective if you miss any green tablets, especially if you miss the first few or the last few green tablets in a pack.

If you miss 1 green tablet:

1. Take the tablet as soon as you remember. Take the next tablet at your regular time. This means you may take 2 tablets in 1 day.
2. You do not need to use a back-up birth control method if you have sex.

If you miss 2 green tablets in a row in week 1 OR week 2 of your pack:

1. Take 2 tablets on the day you remember and 2 tablets the next day.
2. Then take 1 tablet a day until you finish the pack.
3. You could become pregnant if you have sex in the 7 days after you restart your tablets. You must use another birth control method (such as a condom and spermicide) as a back- up for those 7 days.

If you miss 2 green tablets in a row in week 3 or week 4 of your pack:

1. If you are a Day 1 Starter:
  Throw out the rest of the tablet pack and start a new pack that same day.
  If you are a Sunday Starter:
  Keep taking 1 tablet every day until Sunday. On Sunday, throw out the rest of the pack and start a new pack of tablets that same day.
2. You could become pregnant if you have sex in the 7 days after you restart your tablets. You must use another birth control method (such as a condom and spermicide) as a back- up for those 7 days.
3. You may not have your period this month but this is expected. However, if you miss your period 2 months in a row, call your healthcare provider because you might be pregnant.

If you miss 3 or more green tablets in a row during any week:

1. If you are a Day 1 Starter:
  Throw out the rest of the tablet pack and start a new pack that same day.
  If you are a Sunday Starter:
  Keep taking 1 tablet every day until Sunday. On Sunday, throw out the rest of the pack and start a new pack of tablets that same day.
2. You could become pregnant if you have sex on the days when you missed tablets or during the first 7 days after you restart your tablets. You must use another birth control method (such as a condom and spermicide) as a back-up the next time you have sex and for the first 7 days after you restart your tablets.
3. You may not have your period this month but this is expected. However, if you miss your period 2 months in a row, call your healthcare provider because you might be pregnant.

If you miss any of the 4 white tablets in Week 4:

1. Throw away the tablets you missed.
2. Keep taking 1 tablet each day until the pack is empty.
3. You do not need a back-up method.
4. Start the next pack of FEMLYV as scheduled.

Finally, if you are still not sure what to do about the tablets you have missed:

1. Use a back-up method (such as a condom and spermicide) anytime you have sex.
2. Contact your healthcare provider and continue taking 1 active green tablet each day until otherwise directed.

Who should not take FEMLYV?

Your healthcare provider will not give you FEMLYV if you have:

- ever had blood clots in your arms, legs (deep vein thrombosis), lungs (pulmonary embolism), or eyes (retinal thrombosis).
- ever had a stroke.
- ever had a heart attack.
- certain heart valve problems or heart rhythm abnormalities that can cause blood clots to form in the heart.
- an inherited problem with your blood that makes it clot more than normal.
- high blood pressure that medicine cannot control.
- diabetes with kidney, eye, nerve, or blood vessel damage.
- ever had certain kinds of severe migraine headaches with aura, numbness, weakness or changes in vision, or have any migraine headache if you are over age 35.
- ever had breast cancer, which may be sensitive to female hormones.
- liver disease, including liver tumors.
- take any Hepatitis C drug combination containing ombitasvir, paritaprevir, ritonavir, with or without dasabuvir. This may increase levels of the liver enzyme “alanine aminotransferase” (ALT) in the blood.

Also, do not take birth control pills if you:

- smoke and are over 35 years old
- are or think you are pregnant
- have any abnormal bleeding from the vagina

Birth control pills may not be a good choice for you if you have ever had jaundice (yellowing of the skin or eyes) caused by pregnancy, also called cholestasis of pregnancy.

Tell your healthcare provider if you have ever had any of the above conditions (your healthcare provider may recommend another method of birth control).

What else should I know about taking FEMLYV?

Birth control pills do not protect you against any sexually transmitted infection, including HIV, the virus that causes AIDS.

Do not skip any tablets, even if you do not have sex often.

If you miss a period, you could be pregnant. However, some women miss periods or have light periods on birth control pills, even when they are not pregnant. Contact your healthcare provider for advice if you:

- think you are pregnant.
- miss 1 period and have not taken your birth control pills every day.
- miss 2 periods in a row.

Birth control pills should not be taken during pregnancy. However, birth control pills taken by accident during pregnancy are not known to cause birth defects.

You should stop FEMLYV at least 4 weeks before you have surgery and not restart it until at least 2 weeks after the surgery, due to an increased risk of blood clots.

In females who are not breastfeeding, do not start FEMLYV sooner than 4 weeks after giving birth.

If you are breastfeeding, consider another birth control method until you are ready to stop breastfeeding. Birth control pills that contain estrogen, like FEMLYV, may decrease the amount of milk you make. A small amount of the pill's hormones passes into breast milk.

Tell your healthcare provider about all medicines you take, including prescription and over-the-counter medicines, vitamins, and herbal supplements. Some medicines and herbal products may make birth control pills less effective, including:

- barbiturates
- bosentan
- carbamazepine
- felbamate
- griseofulvin
- oxcarbazepine
- phenytoin
- rifampicin
- St. John’s wort
- topiramate

Use a back-up or alternative birth control method when you take medicines that may make birth control pills less effective.

Birth control pills may interact with lamotrigine, an anticonvulsant used for epilepsy. This may increase the risk of seizures, so your healthcare provider may need to adjust the dose of lamotrigine.

If you have vomiting or diarrhea, your birth control pills may not work as well. Use another birth control method, like a condom and spermicide, until you check with your healthcare provider.

Women on thyroid hormone replacement therapy may need increased doses of thyroid hormone.

If you are scheduled for any laboratory tests, tell your healthcare provider that you are taking birth control pills. Certain blood tests may be affected by birth control pills.

What are the most serious risks of taking FEMLYV?

Like pregnancy, birth control pills increase the risk of serious blood clots, especially in women who have other risk factors, such as smoking, obesity, or age greater than 35. This increased risk is highest when you first start taking birth control pills and when you restart the same or different birth control pills after not using them for a month or more.

It is possible to die from a problem caused by a blood clot, such as a heart attack or a stroke.

Some examples of serious blood clots are blood clots in the:

- legs (deep vein thrombosis)
- lungs (pulmonary embolus)
- eyes (loss of eyesight)
- heart (heart attack)
- brain (stroke)

Women who take birth control pills may get:

- high blood pressure
- gallbladder problems
- rare cancerous or noncancerous liver tumors.

All of these events are uncommon in healthy women.

Call your healthcare provider right away if you have:

- leg pain that does not go away
- sudden shortness of breath
- sudden blindness, partial or complete
- severe pain or pressure in your chest
- sudden, severe headache unlike your usual headaches
- weakness or numbness in an arm or leg, or trouble speaking
- yellowing of the skin or eyeballs

What are the common side effects of birth control pills?

The most common side effects of birth control pills are:

- spotting or bleeding between menstrual periods
- nausea
- breast tenderness
- headache

These side effects are usually mild and usually disappear with time.

Less common side effects are:

- acne
- less sexual desire
- bloating or fluid retention
- blotchy darkening of the skin, especially on the face
- high blood sugar, especially in women who already have diabetes
- high fat (cholesterol, triglyceride) levels in the blood
- depression, especially if you have had depression in the past. Call your healthcare provider immediately if you have any thoughts of harming yourself
- problems tolerating contact lenses
- weight gain

These are not all the possible side effects of FEMLYV. For more information, ask your healthcare provider or pharmacist. Call your doctor for medical advice about side effects. You may report side effects to FDA at 1-800-FDA-1088.

No serious problems have been reported from a birth control pill overdose, even when accidentally taken by children.

Do birth control pills cause cancer?

It is not known if hormonal birth control pills cause breast cancer. Some studies, but not all, suggest that there could be a slight increase in the risk of breast cancer among current users with longer duration of use.

If you have breast cancer now, or have had it in the past, do not use hormonal birth control because some breast cancers are sensitive to hormones.

Women who use birth control pills may have a slightly higher chance of getting cervical cancer. However, this may be due to other reasons such as having more sexual partners.

What should I know about my period when taking FEMLYV?

Irregular vaginal bleeding or spotting may occur while you are taking FEMLYV. Irregular bleeding may vary from slight staining between menstrual periods to breakthrough bleeding, which is a flow much like a regular period. Irregular bleeding occurs most often during the first few months of oral contraceptive use, but may also occur after you have been taking the pill for some time. Such bleeding may be temporary and usually does not indicate any serious problems. It is important to continue taking your tablets on schedule. If the bleeding occurs in more than one cycle, is unusually heavy, or lasts for more than a few days, call your healthcare provider.

Some women may not have a menstrual period but this should not be cause for alarm as long as you have taken the tablets according to direction.

What if I miss my scheduled period when taking FEMLYV?

It is not uncommon to miss your period. However, if you go 2 or more months in a row without a period, or you miss your period after a month where you did not take all your tablets correctly, call your healthcare provider because you may be pregnant. Also notify your healthcare provider if you have symptoms of pregnancy such as morning sickness or unusual breast tenderness. Stop taking FEMLYV if you are pregnant.

What if I want to become pregnant?

You may stop taking the tablets whenever you wish. Consider a visit with your healthcare provider for a pre-pregnancy checkup before you stop taking the tablets.

General advice about FEMLYV

Your healthcare provider prescribed FEMLYV for you. Please do not share FEMLYV with anyone else. Keep FEMLYV out of the reach of children.

Store FEMLYV at room temperature between 68°F to 77º F (20°C to 25º C).

If you have concerns or questions, ask your healthcare provider. You may also ask your pharmacist for a more detailed label written for healthcare professionals.

For all medical inquiries contact:
Millicent
Medical Communications 1-877-810-2101

Distributed by:
Millicent U.S., Inc., East Hanover, NJ 07936
© 2024 Millicent. All rights reserved.
FEMLYV™ and its design are trademarks of Millicent Puerto Rico LLC.

This Patient Information has been approved by the Food and Drug Administration.

Approved: 12/2024

PACKAGE/LABEL PRINCIPAL DISPLAY PANEL – Carton Label

FEMLYV™

(norethindrone acetate and
ethinyl estradiol
orally disintegrating tablets)

1mg/0.02mg

NDC Number 72495-601-84

FEMLYV™
28-day regimen
Each blister provides
24 days of active therapy

Rx only

This package contains
3 blister cards of
28 orally disintegrating
tablets (ODTs) each

Millicent Pharma®

PACKAGE/LABEL PRINCIPAL DISPLAY PANEL – Pouch Label

NDC 72495-601-84

FEMLYV™

(norethindrone acetate and
ethinyl estradiol
orally disintegrating tablets)

1mg/0.02mg

FEMLYV™ 28-day regimen
Each blister provides
24 days of active therapy

Rx only

This package contains 1 blister card
of 28 orally disintegrating
tablets (ODTs)

Millicent Pharma®

PACKAGE/LABEL PRINCIPAL DISPLAY PANEL – Blister Card Label

FEMLYV™

(norethindrone acetate and ethinyl estradiol orally disintegrating tablets)

1mg/0.02mg

RX only

Millicent Pharma®

PACKAGE/LABEL PRINCIPAL DISPLAY PANEL – Sample Carton Label

FEMLYV™

(norethindrone acetate and
ethinyl estradiol
orally disintegrating tablets)

1mg/0.02mg

NDC Number 72495-601-28

Physician’s Sample –
Not For Sale

FEMLYV™
28-day regimen
Each blister provides
24 days of active therapy

Rx only

This package contains
1 blister card of 28 orally
disintegrating tablets (ODTs)

Millicent Pharma®

PACKAGE/LABEL PRINCIPAL DISPLAY PANEL – Sample Pouch Label

NDC 72495-601-28

FEMLYV™

(norethindrone acetate and
ethinyl estradiol
orally disintegrating tablets)

1mg/0.02mg

Physician’s Sample – Not For Sale

FEMLYV™ 28-day regimen
Each blister provides
24 days of active therapy

Rx only

This package contains 1 blister card
of 28 orally disintegrating
tablets (ODTs)

Millicent Pharma®